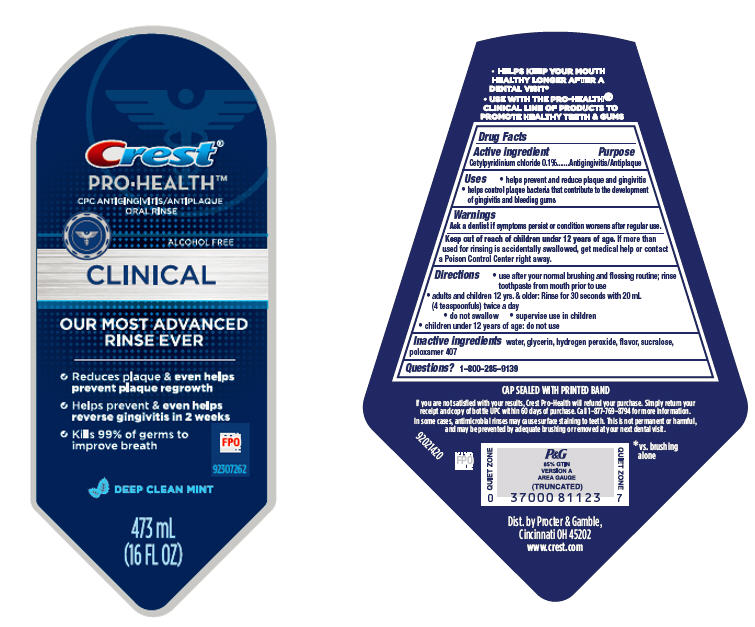 DRUG LABEL: Crest Pro-Health
NDC: 37000-843 | Form: RINSE
Manufacturer: The Procter & Gamble Manufacturing Company
Category: otc | Type: HUMAN OTC DRUG LABEL
Date: 20250731

ACTIVE INGREDIENTS: CETYLPYRIDINIUM CHLORIDE 0.02 g/20 mL
INACTIVE INGREDIENTS: GLYCERIN; HYDROGEN PEROXIDE; SUCRALOSE; POLOXAMER 407; WATER

Crest® Pro-Health™
Clinical

Drug Facts

Active ingredient

Cetylpyridinium chloride 0.1%

Purpose

Antigingivitis/Antiplaque

Uses

- helps prevent and reduce plaque and gingivitis
- helps control plaque bacteria that contribute to the development of gingivitis and bleeding gums

Warnings

ASK DOCTOR/PHARMACIST

Ask a dentist if symptoms persist or condition worsens after regular use.

Keep out of reach of children under 12 years of age. If more than used for rinsing is accidentally swallowed, get medical help or contact a Poison Control Center right away.

Directions

- use after your normal brushing and flossing routine; rinse toothpaste from mouth prior to use
- adults and children 12 yrs. & older: Rinse for 30 seconds with 20 mL (4 teaspoonfuls) twice a day
  - do not swallow
  - supervise use in children
- children under 12 years of age: do not use

Inactive ingredients

water, glycerin, hydrogen peroxide, flavor, sucralose, poloxamer 407

Questions?

1–800–285–9139

Dist. by Procter & Gamble,
Cincinnati OH 45202

PRINCIPAL DISPLAY PANEL - 473 mL Bottle Label

Crest®
PRO-HEALTH™
CPC ANTIGINGIVITIS/ANTIPLAQUE
ORAL RINSE

ALCOHOL FREE

CLINICAL

OUR MOST ADVANCED RINSE EVER

- Reduces plaque & even helps prevent plaque regrowth
- Helps prevent & even helps reverse gingivitis in 2 weeks
- Kills 99% of germs to improve breath

DEEP CLEAN MINT

473mL
(16 FL OZ)